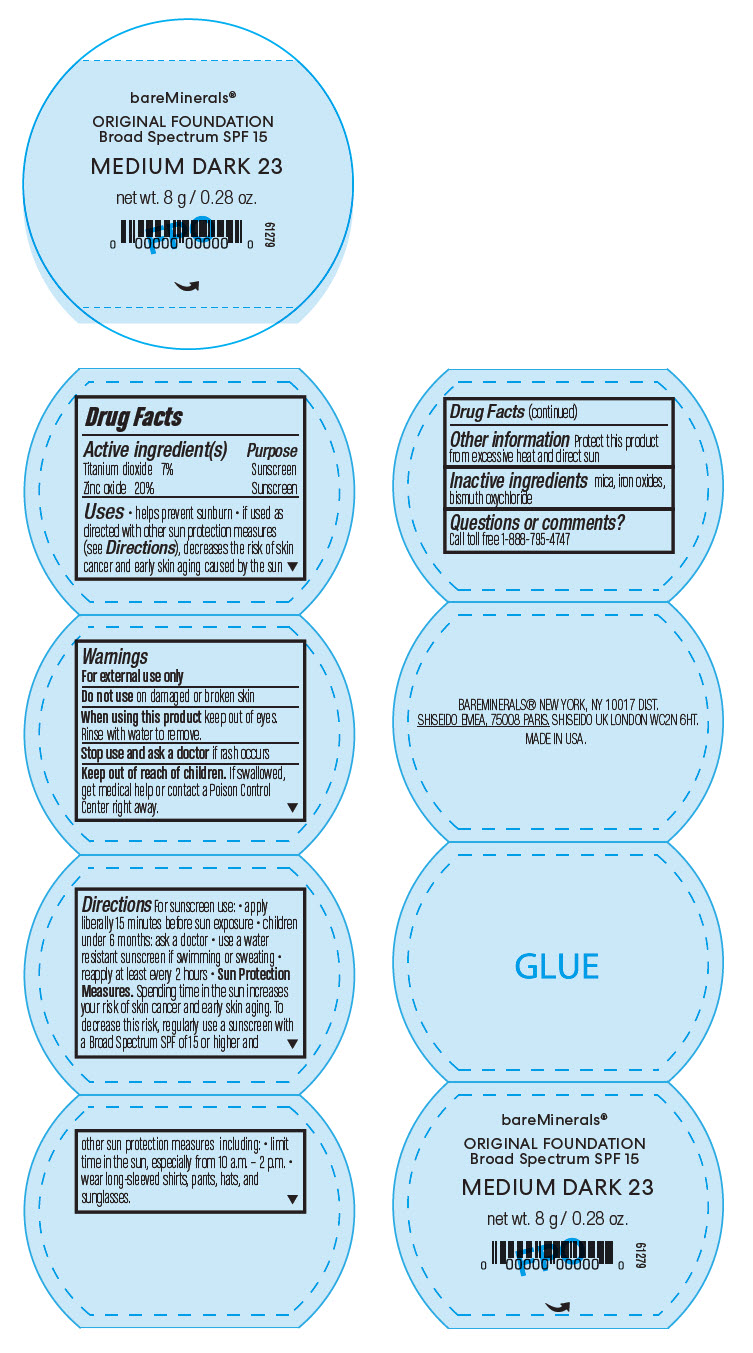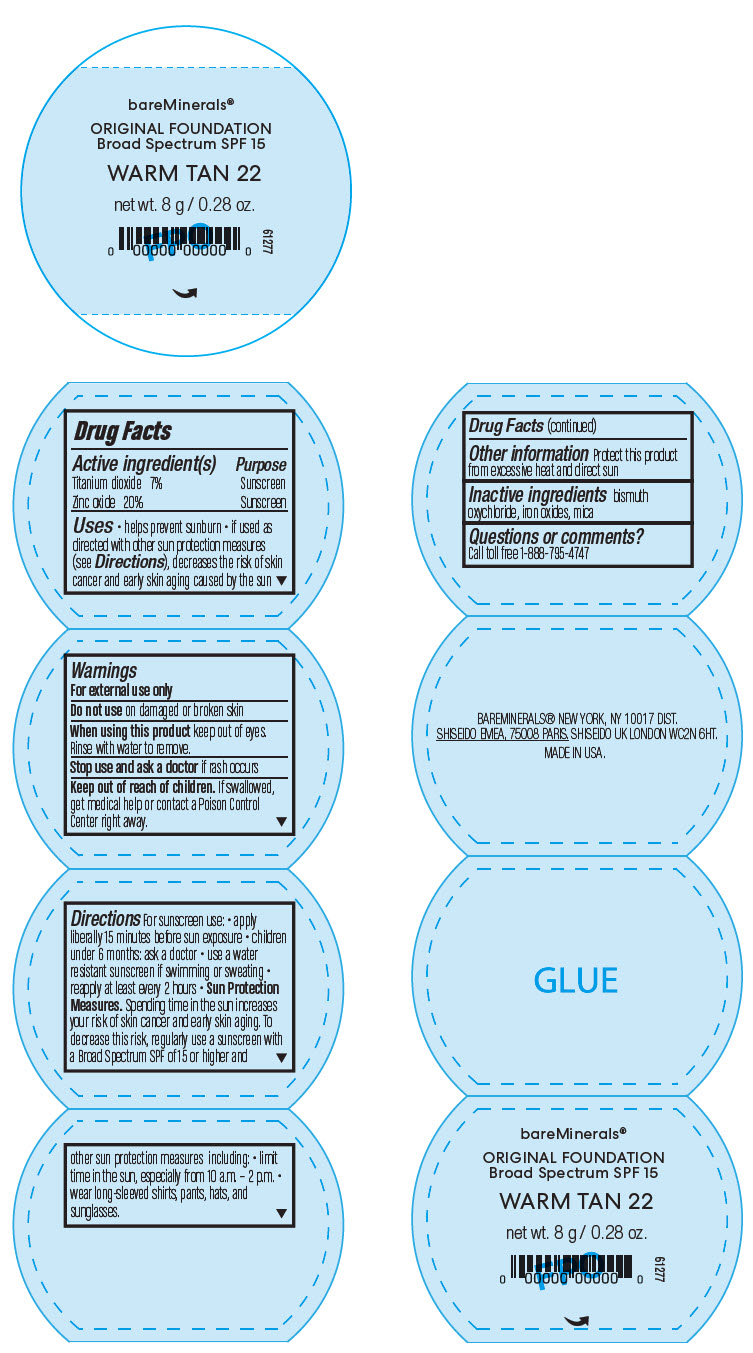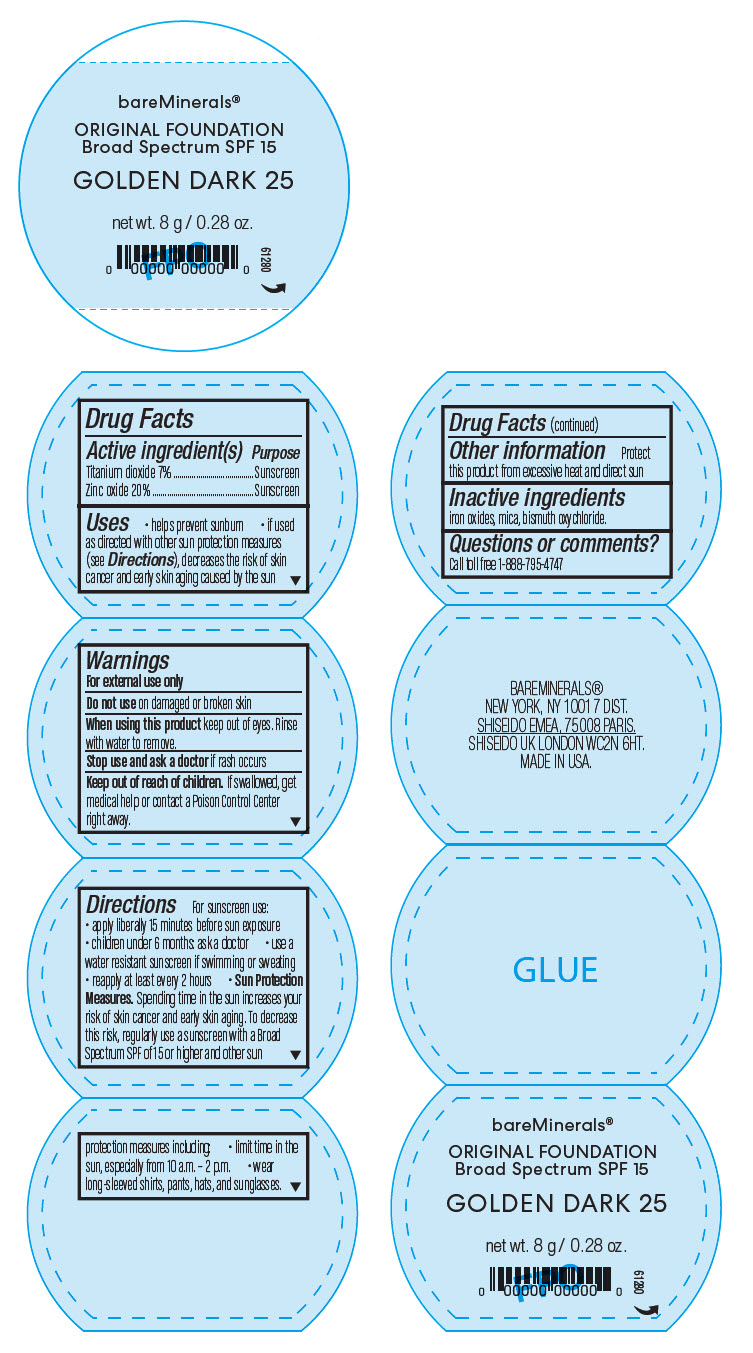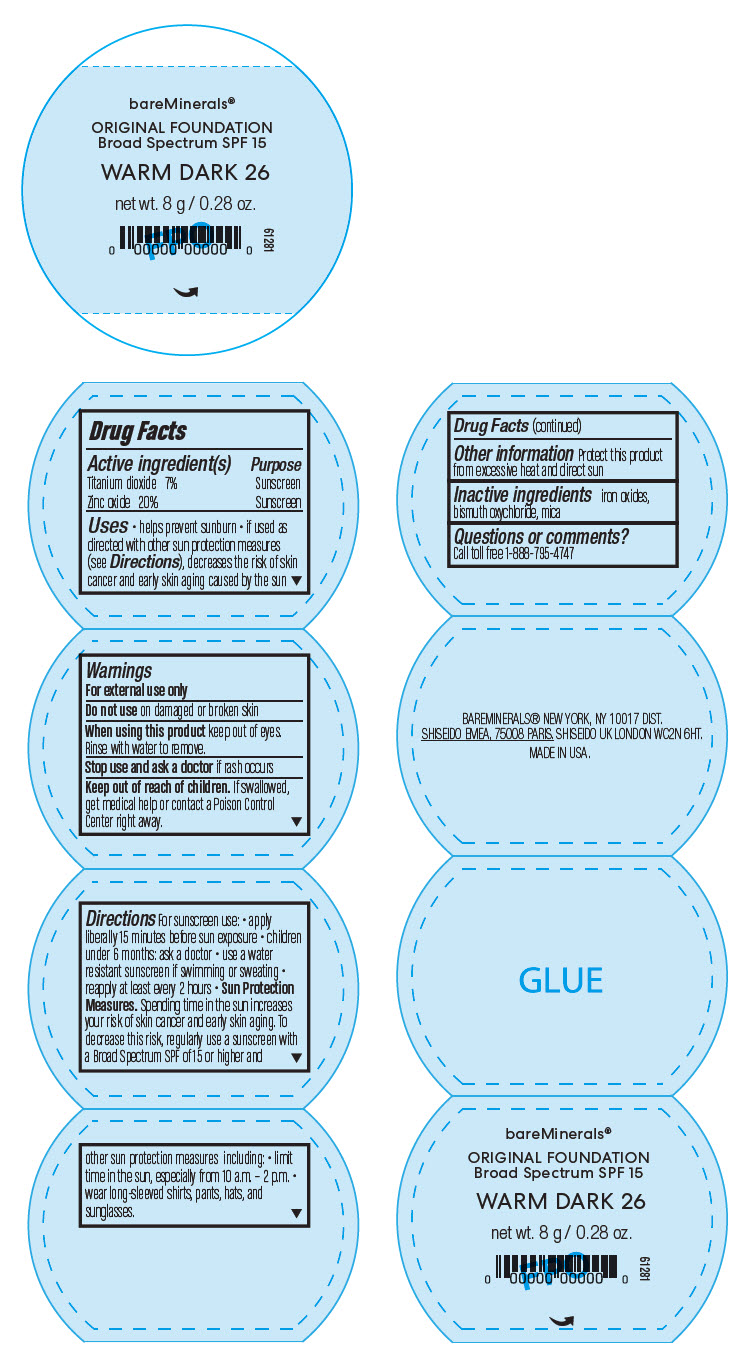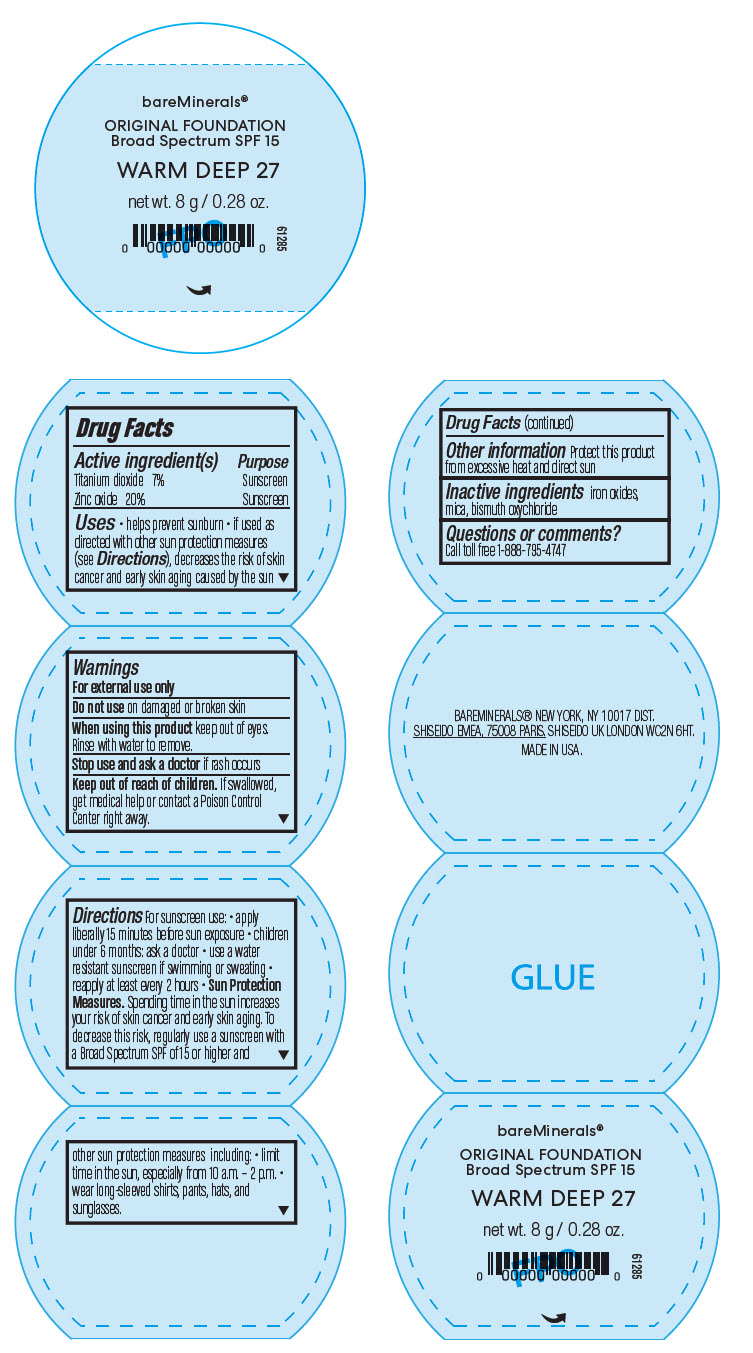 DRUG LABEL: bareMinerals Original Foundation Broad Spectrum SPF 15
NDC: 98132-015 | Form: POWDER
Manufacturer: Orveon Global US LLC
Category: otc | Type: HUMAN OTC DRUG LABEL
Date: 20231004

ACTIVE INGREDIENTS: TITANIUM DIOXIDE 560 mg/8 g; ZINC OXIDE 1600 mg/8 g
INACTIVE INGREDIENTS: MICA; FERRIC OXIDE RED; BISMUTH OXYCHLORIDE

bareMinerals® Original Foundation Broad Spectrum SPF 15

Drug Facts

ACTIVE INGREDIENT

Active ingredient(s) | Purpose
Titanium dioxide 7% | Sunscreen
Zinc oxide 20% | Sunscreen

Uses

- helps prevent sunburn
- if used as directed with other sun protection measures (see Directions), decreases the risk of skin cancer and early skin aging caused by the sun

Warnings

For external use only

Do not use on damaged or broken skin

When using this product keep out of eyes. Rinse with water to remove.

Stop use and ask a doctor if rash occurs

Keep out of reach of children. If swallowed, get medical help or contact a Poison Control Center right away.

Directions

For sunscreen use:

- apply liberally 15 minutes before sun exposure
- children under 6 months: ask a doctor
- use a water resistant sunscreen if swimming or sweating
- reapply at least every 2 hours
- Sun Protection Measures. Spending time in the sun increases your risk of skin cancer and early skin aging. To decrease this risk, regularly use a sunscreen with a Broad Spectrum SPF of 15 or higher and other sun protection measures including:
  - limit time in the sun, especially from 10 a.m. – 2 p.m.
  - wear long-sleeved shirts, pants, hats, and sunglasses.

Other information

Protect this product from excessive heat and direct sun

Inactive ingredients

bismuth oxychloride, iron oxides, mica

Questions or comments?

Call toll free 1-888-795-4747

PRINCIPAL DISPLAY PANEL - 8 g Jar Label - Medium Dark 23

bareMinerals®

ORIGINAL FOUNDATION
Broad Spectrum SPF 15

MEDIUM DARK 23

net wt. 8 g / 0.28 oz.

61279

PRINCIPAL DISPLAY PANEL - 8 g Jar Label - Warm Tan 22

bareMinerals®

ORIGINAL FOUNDATION
Broad Spectrum SPF 15

WARM TAN 22

net wt. 8 g / 0.28 oz.

61277

PRINCIPAL DISPLAY PANEL - 8 g Jar Label - Golden Dark 25

bareMinerals®

ORIGINAL FOUNDATION
Broad Spectrum SPF 15

GOLDEN DARK 25

net wt. 8 g / 0.28 oz.

61280

PRINCIPAL DISPLAY PANEL - 8 g Jar Label - Warm Dark 26

bareMinerals®

ORIGINAL FOUNDATION
Broad Spectrum SPF 15

WARM DARK 26

net wt. 8 g / 0.28 oz.

61281

PRINCIPAL DISPLAY PANEL - 8 g Jar Label - Warm Deep 27

bareMinerals®

ORIGINAL FOUNDATION
Broad Spectrum SPF 15

WARM DEEP 27

net wt. 8 g / 0.28 oz.

61285